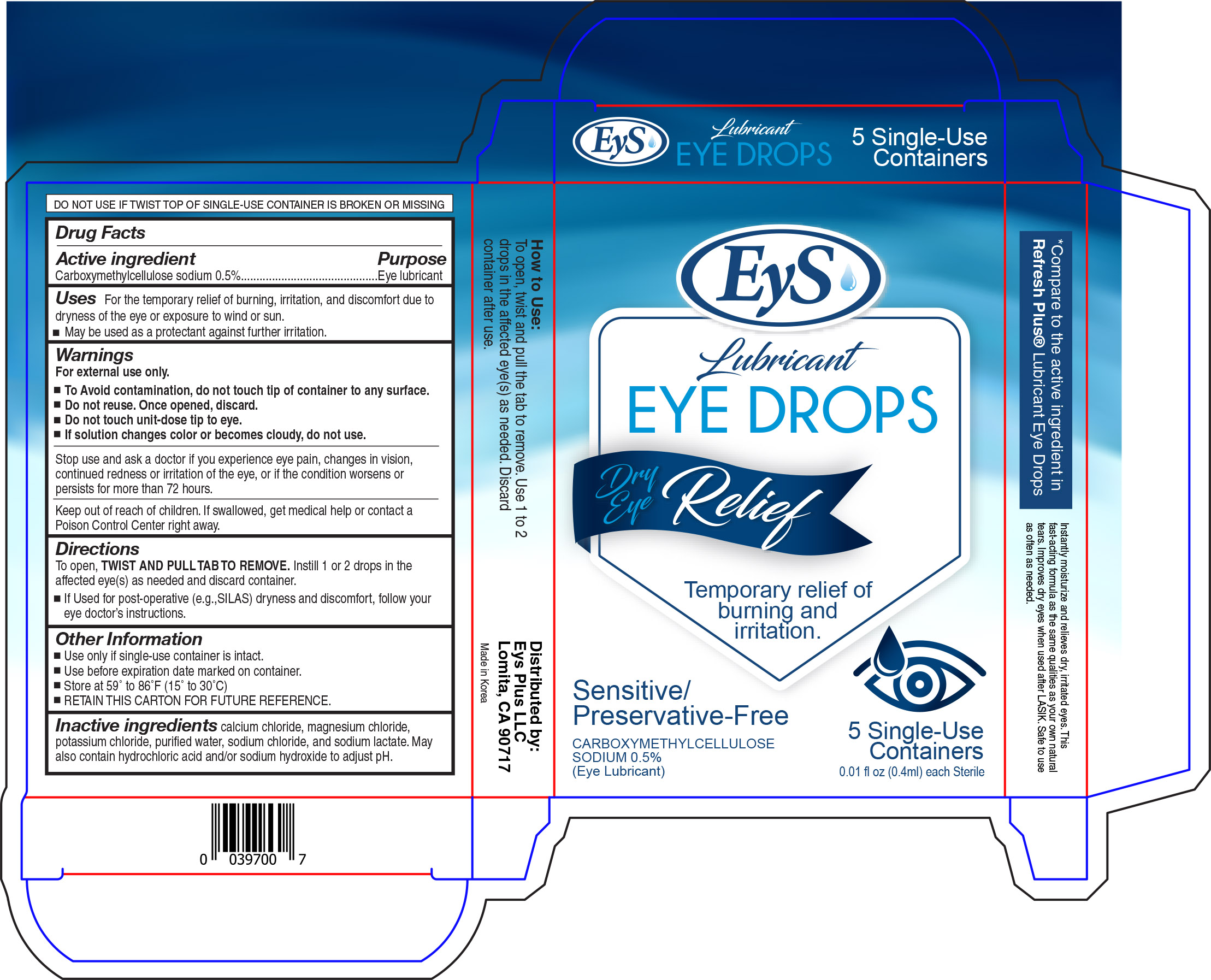 DRUG LABEL: EyS-ED
NDC: 57349-397 | Form: SOLUTION/ DROPS
Manufacturer: Eyes-Plus LLC
Category: otc | Type: HUMAN OTC DRUG LABEL
Date: 20180613

ACTIVE INGREDIENTS: CARBOXYMETHYLCELLULOSE SODIUM 5 mg/1 mL
INACTIVE INGREDIENTS: SODIUM CHLORIDE; SODIUM LACTATE; POTASSIUM CHLORIDE; WATER; MAGNESIUM CHLORIDE; CALCIUM CHLORIDE

Eys Lubricant Eye Drops Single Use

Active ingredient Purpose

Carboxymethylcellulose sodium 0.5%...............Eye lubricant

Uses

For the temporary relief of burning, irritation, and discomfort due to dryness of the eye or exposure to wind or sun.

- May be used as a protectant against further irritation

Warnings

For external use only

- To avoid contamination, do not touch tip of container to any surface.
- Do not reuse. Once opened, discard.
- Do not touch unit does tip to eye.
- If solution changes color or becomes cloudy, do not use.

Stop use and ask a doctor if you experience eye pain, changes in vision, continued redness or irritation of the eye, or if the condtion worsens or persists for more than 72 hours.

Keep out of reach of children. If swallowed, get medical help or contact a Poison Control Center right away.

Directions

To open, TWIST AND PULL TAB TO REMOVE. Instill 1 or 2 drops in the affected eye(s) as needed and discard container.

- If used for post-operative (e.g., SILAS) dryness and discomfort, follow your eye doctor's instructions.

Other Information

- Use only if single-use container is intact.
- Use before expiration date marked on container.
- Store at 59° to 86°F (15° to 30°C)
- RETAIN THIS CARTON FOR FUTURE REFERENCE.

Inactive ingredients

calcium chloride, magnesium chloride, potassium chloride, purified water, sodium chloride, and sodium lactate. May also contain hydrochloric acid and/or sodium hydroxide to adjust pH.

DOSAGE AND ADMINISTRATION

Distributed by:

Eys Plus LLC

Lomita, CA 90717'

Made in Korea